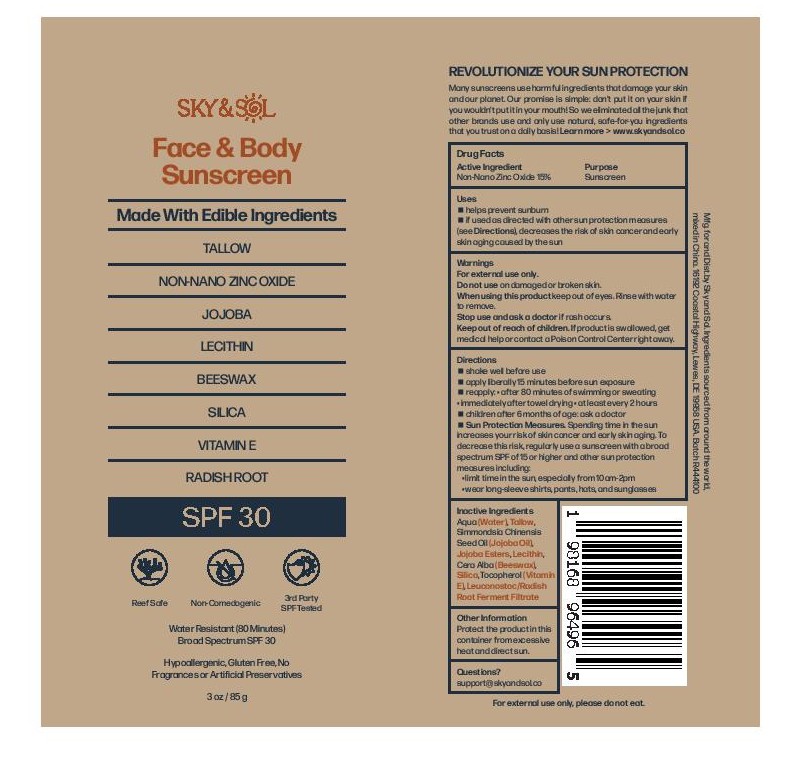 DRUG LABEL: Sky and Sol Face and Body Sunscreen SPF30
NDC: 84632-3030 | Form: CREAM
Manufacturer: Delta Ecommerce LLC
Category: otc | Type: HUMAN OTC DRUG LABEL
Date: 20251230

ACTIVE INGREDIENTS: ZINC OXIDE 25 g/100 g
INACTIVE INGREDIENTS: ASTAXANTHIN; PINUS STROBUS BARK; AQUA; JOJOBA OIL; LEUCONOSTOC/RADISH ROOT FERMENT FILTRATE; BEESWAX; TAPIOCA STARCH; TALLOW; LECITHIN, SUNFLOWER; HYDROLYZED JOJOBA ESTERS (ACID FORM)

PURPOSE

Sunscreen

INDICATIONS AND USAGE

helps prevent sunburn; if used as directed with other sun protection measures (see Directions), decreases the risk of skin cancer and early skin aging caused by the sun

DOSAGE AND ADMINISTRATION

Shake well before use.
Apply liberally 15 minutes before sun exposure.
Reapply:
after 80 minutes of swimming or sweating
immediately after towel drying
at least every 2 hours

WARNINGS

For external use only.
Do not use on damaged or broken skin.
Stop use and ask a doctor if rash occurs.
When using this product, keep out of eyes. Rinse with water to remove.

Keep out of reach of children. If swallowed, get medical help or contact a Poison Control Center right away.

INACTIVE INGREDIENT

Aqua (Water), Tallow, Simmondsia Chinensis (Jojoba) Seed Oil, Jojoba Esters, Lecithin, Cera Alba (Beeswax), Silica, Tocopherol (Vitamin E), Leuconostoc/Radish Root Ferment Filtrate